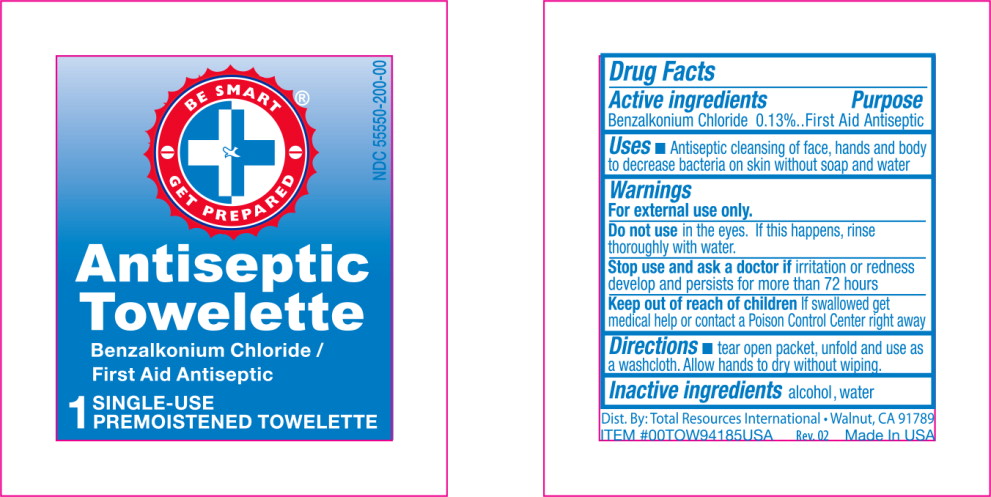 DRUG LABEL: Antiseptic
NDC: 55550-200 | Form: LIQUID
Manufacturer: Total Resources International
Category: otc | Type: HUMAN OTC DRUG LABEL
Date: 20130701

ACTIVE INGREDIENTS: benzalkonium chloride 1.3 mg/1 mL
INACTIVE INGREDIENTS: alcohol; water

Drug Facts

Active ingredients

Benzalkonium Chloride 0.13%

Purpose

First Aid Antiseptic

Uses

- Antiseptic cleansing of face, hands and body to decrease bacteria on skin without soap and water

Warnings

For external use only

Do not use in the eyes. If this happens, rinse thoroughly with water.

Stop use and ask doctor if irritation or redness develop and persists for more than 72 hours

Keep out of reach of children If swallowed, get medical help or contact a Poison Control Center right away

Directions

- tear open packet, unfold and use as a washcloth. Allow hands to dry without wiping.

Inactive ingredients

alcohol, water

PRINCIPAL DISPLAY PANEL – packet label

NDC 55550-200-00

Antiseptic
Towelette
Benzalkonium Chloride/
First Aid Antiseptic
1 SINGLE-USE
PREMOISTENED TOWELETTE